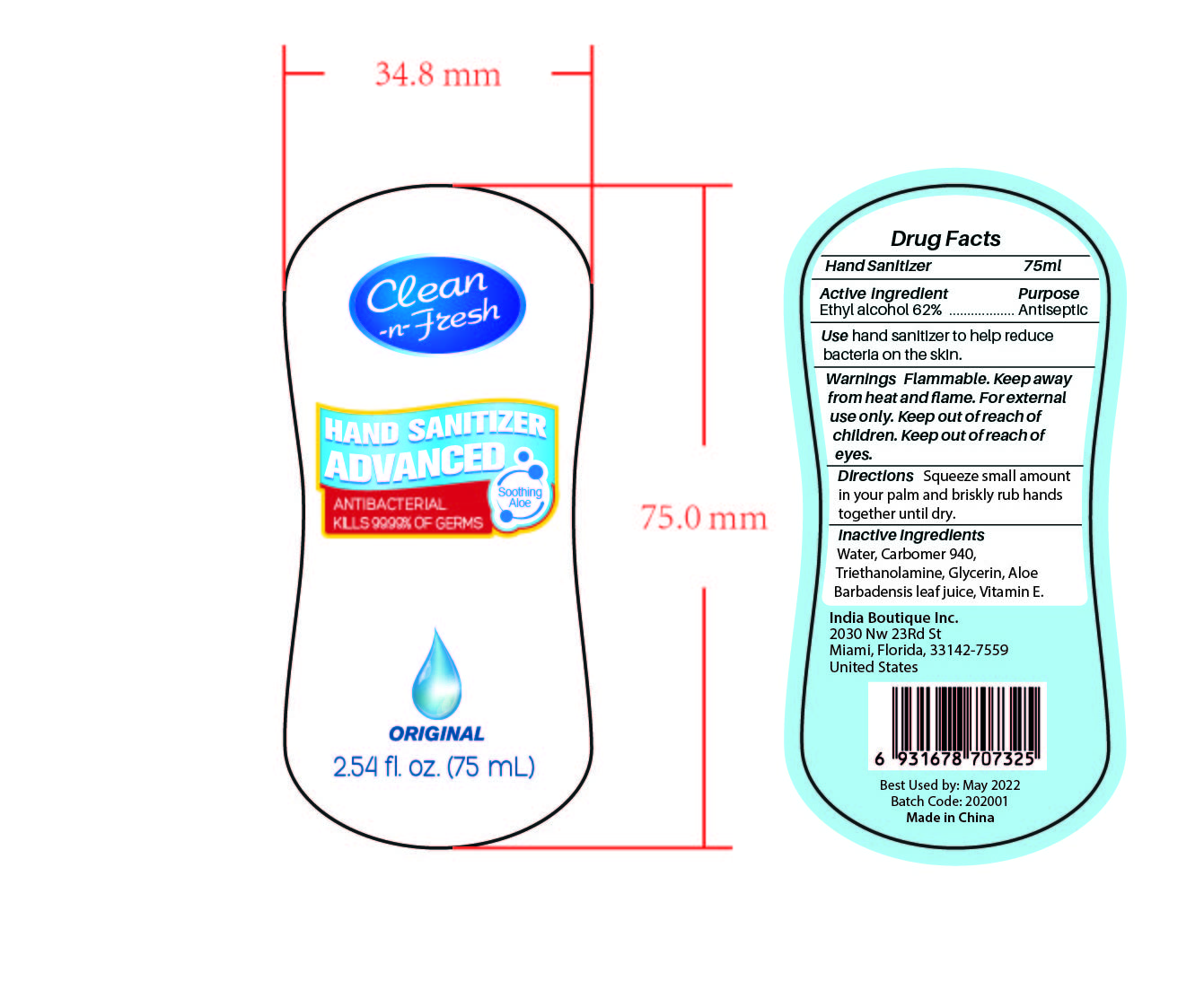 DRUG LABEL: Clean-n-Fresh
NDC: 74326-620 | Form: GEL
Manufacturer: INDIA BOUTIQUE INC
Category: otc | Type: HUMAN OTC DRUG LABEL
Date: 20200425

ACTIVE INGREDIENTS: ALCOHOL 62 mL/100 mL
INACTIVE INGREDIENTS: ALOE VERA LEAF; TRIETHANOLAMINE DODECYLBENZENESULFONATE; GLYCERIN; CARBOMER 940; WATER; ALPHA-TOCOPHEROL

Active Ingredient(s)

Alcohol 62% v/v. Purpose: Antiseptic

Purpose

Antiseptic, Hand Sanitizer

Use

Hand sanitizer to help reduce bacteria on the skin

Warnings

Flammable. Keep away from fire or flame.

Do not use

Keep out of reach of eyes.

When using this product keep out of eyes, ears, and mouth. In case of contact with eyes, rinse eyes thoroughly with water.
Stop use and ask a doctor if irritation or rash occurs. These may be signs of a serious condition.
Keep out of reach of children. If swallowed, get medical help or contact a Poison Control Center right away.

Keep out of reach of children.

Directions

Squeeze small amount in your palm and briskly rub hands together until dry.

Inactive ingredients

Water,Carbomer 940,Triethanolamine,Glycerin,Aloe Barbadensis leaf juice, Vitamin E

Package Label - Principal Display Panel

75 mL NDC: 74326-620-75